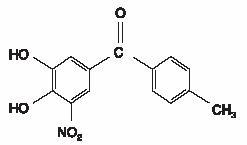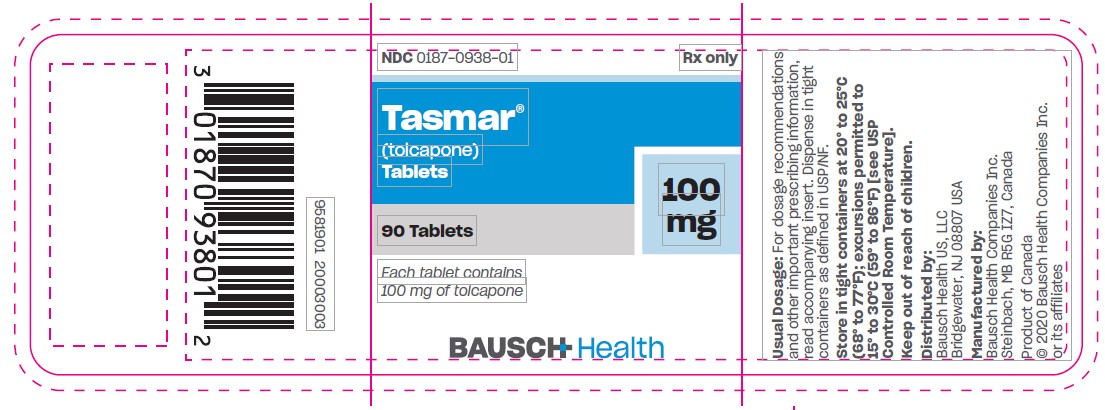 DRUG LABEL: Tasmar
NDC: 0187-0938 | Form: TABLET, FILM COATED
Manufacturer: Bausch Health US LLC
Category: prescription | Type: HUMAN PRESCRIPTION DRUG LABEL
Date: 20201002

ACTIVE INGREDIENTS: Tolcapone 100 mg/1 1
INACTIVE INGREDIENTS: MICROCRYSTALLINE CELLULOSE; Lactose Monohydrate; ANHYDROUS DIBASIC CALCIUM PHOSPHATE; sodium starch glycolate type a potato; povidone K30; talc; magnesium stearate; WATER; HYPROMELLOSE, UNSPECIFIED; titanium dioxide; triacetin; sodium lauryl sulfate; ferric oxide yellow; ferric oxide red; ETHYLCELLULOSE, UNSPECIFIED

TASMAR®
(tolcapone)
Tablets 100 mg

Before prescribing TASMAR®, the physician should be thoroughly familiar with the details of this prescribing information.

TASMAR SHOULD NOT BE USED BY PATIENTS UNTIL THERE HAS BEEN A COMPLETE DISCUSSION OF THE RISKS AND THE PATIENT HAS PROVIDED WRITTEN ACKNOWLEDGEMENT THAT THE RISKS HAVE BEEN EXPLAINED (SEE PATIENT ACKNOWLEDGEMENT OF RISKS SECTION).

WARNING

Because of the risk of potentially fatal, acute fulminant liver failure, TASMAR (tolcapone) should ordinarily be used in patients with Parkinson's disease on l-dopa/carbidopa who are experiencing symptom fluctuations and are not responding satisfactorily to or are not appropriate candidates for other adjunctive therapies (see INDICATIONS and DOSAGE AND ADMINISTRATION sections).

Because of the risk of liver injury and because TASMAR, when it is effective, provides an observable symptomatic benefit, the patient who fails to show substantial clinical benefit within 3 weeks of initiation of treatment, should be withdrawn from TASMAR.

TASMAR therapy should not be initiated if the patient exhibits clinical evidence of liver disease or two SGPT/ALT or SGOT/AST values greater than the upper limit of normal. Patients with severe dyskinesia or dystonia should be treated with caution (see PRECAUTIONS: Rhabdomyolysis).

PATIENTS WHO DEVELOP EVIDENCE OF HEPATOCELLULAR INJURY WHILE ON TASMAR AND ARE WITHDRAWN FROM THE DRUG FOR ANY REASON MAY BE AT INCREASED RISK FOR LIVER INJURY IF TASMAR IS REINTRODUCED. ACCORDINGLY, SUCH PATIENTS SHOULD NOT ORDINARILY BE CONSIDERED FOR RETREATMENT.

Cases of severe hepatocellular injury, including fulminant liver failure resulting in death, have been reported in postmarketing use. As of May 2005, three cases of fatal fulminant hepatic failure have been reported from more than 40,000 patient years of worldwide use. This incidence may be 10- to 100-fold higher than the background incidence in the general population. Underreporting of cases may lead to significant underestimation of the increased risk associated with the use of TASMAR. All three cases were reported within the first six months of initiation of treatment with TASMAR. Analysis of the laboratory monitoring data in over 3,400 TASMAR-treated patients participating in clinical trials indicated that increases in SGPT/ALT or SGOT/AST, when present, generally occurred within the first 6 months of treatment with TASMAR.

A prescriber who elects to use TASMAR in face of the increased risk of liver injury is strongly advised to monitor patients for evidence of emergent liver injury. Patients should be advised of the need for self-monitoring for both the classical signs of liver disease (e.g., clay colored stools, jaundice) and the nonspecific ones (e.g., fatigue, loss of appetite, lethargy).

Although a program of periodic laboratory monitoring for evidence of hepatocellular injury is recommended, it is not clear that periodic monitoring of liver enzymes will prevent the occurrence of fulminant liver failure. However, it is generally believed that early detection of drug-induced hepatic injury along with immediate withdrawal of the suspect drug enhances the likelihood for recovery. Accordingly, the following liver monitoring program is recommended.

Before starting treatment with TASMAR, the physician should conduct appropriate tests to exclude the presence of liver disease. In patients determined to be appropriate candidates for treatment with TASMAR, serum glutamic-pyruvic transaminase (SGPT/ALT) and serum glutamic-oxaloacetic transaminase (SGOT/AST) levels should be determined at baseline and periodically (i.e., every 2 to 4 weeks) for the first 6 months of therapy. After the first six months, periodic monitoring is recommended at intervals deemed clinically relevant. Although more frequent monitoring increases the chances of early detection, the precise schedule for monitoring is a matter of clinical judgment. If the dose is increased to 200 mg tid (see DOSAGE AND ADMINISTRATION section), liver enzyme monitoring should take place before increasing the dose and then be conducted every 2 to 4 weeks for the following 6 months of therapy. After six months, periodic monitoring is recommended at intervals deemed clinically relevant.

TASMAR should be discontinued if SGPT/ALT or SGOT/AST levels exceed 2 times the upper limit of normal or if clinical signs and symptoms suggest the onset of hepatic dysfunction (persistent nausea, fatigue, lethargy, anorexia, jaundice, dark urine, pruritus, and right upper quadrant tenderness).

DESCRIPTION:

TASMAR is available as tablets containing 100 mg tolcapone.

Tolcapone, an inhibitor of catechol-O-methyltransferase (COMT), is used in the treatment of Parkinson's disease as an adjunct to levodopa/carbidopa therapy. It is a yellow, odorless, non-hygroscopic, crystalline compound with a relative molecular mass of 273.25. The chemical name of tolcapone is 3,4-dihydroxy-4'-methyl-5-nitrobenzophenone. Its empirical formula is C14H11NO5 and its structural formula is:

Inactive ingredients: Core: microcrystalline cellulose, lactose monohydrate, anhydrous dibasic calcium phosphate, sodium starch glycolate, povidone, talc, magnesium stearate, and purified water. Film Coating: hypromellose, titanium dioxide, talc, ethylcellulose, triacetin, sodium lauryl sulfate, yellow iron oxide, red iron oxide, and purified water.

CLINICAL PHARMACOLOGY:

Mechanism of Action:

Tolcapone is a selective and reversible inhibitor of catechol-O-methyltransferase (COMT).

In mammals, COMT is distributed throughout various organs. The highest activities are in the liver and kidney. COMT also occurs in the heart, lung, smooth and skeletal muscles, intestinal tract, reproductive organs, various glands, adipose tissue, skin, blood cells and neuronal tissues, especially in glial cells. COMT catalyzes the transfer of the methyl group of S-adenosyl-L-methionine to the phenolic group of substrates that contain a catechol structure. Physiological substrates of COMT include dopa, catecholamines (dopamine, norepinephrine, epinephrine) and their hydroxylated metabolites. The function of COMT is the elimination of biologically active catechols and some other hydroxylated metabolites. In the presence of a decarboxylase inhibitor, COMT becomes the major metabolizing enzyme for levodopa catalyzing the metabolism to 3-methoxy-4-hydroxy-L-phenylalanine (3-OMD) in the brain and periphery.

The precise mechanism of action of tolcapone is unknown, but it is believed to be related to its ability to inhibit COMT and alter the plasma pharmacokinetics of levodopa. When tolcapone is given in conjunction with levodopa and an aromatic amino acid decarboxylase inhibitor, such as carbidopa, plasma levels of levodopa are more sustained than after administration of levodopa and an aromatic amino acid decarboxylase inhibitor alone. It is believed that these sustained plasma levels of levodopa result in more constant dopaminergic stimulation in the brain, leading to greater effects on the signs and symptoms of Parkinson's disease in patients as well as increased levodopa adverse effects, sometimes requiring a decrease in the dose of levodopa. Tolcapone enters the CNS to a minimal extent, but has been shown to inhibit central COMT activity in animals.

Pharmacodynamics:

COMT Activity in Erythrocytes:

Studies in healthy volunteers have shown that tolcapone reversibly inhibits human erythrocyte catechol-O-methyltransferase (COMT) activity after oral administration. The inhibition is closely related to plasma tolcapone concentrations. With a 200-mg single dose of tolcapone, maximum inhibition of erythrocyte COMT activity is on average greater than 80%. During multiple dosing with tolcapone (200 mg tid), erythrocyte COMT inhibition at trough tolcapone blood concentrations is 30% to 45%.

Effect on the Pharmacokinetics of Levodopa and its Metabolites:

When tolcapone is administered together with levodopa/carbidopa, it increases the relative bioavailability (AUC) of levodopa by approximately twofold. This is due to a decrease in levodopa clearance resulting in a prolongation of the terminal elimination half-life of levodopa (from approximately 2 hours to 3.5 hours). In general, the average peak levodopa plasma concentration (Cmax) and the time of its occurrence (Tmax) are unaffected. The onset of effect occurs after the first administration and is maintained during long-term treatment. Studies in healthy volunteers and Parkinson's disease patients have confirmed that the maximal effect occurs with 100 mg to 200 mg tolcapone. Plasma levels of 3-OMD are markedly and dose-dependently decreased by tolcapone when given with levodopa/carbidopa.

Population pharmacokinetic analyses in patients with Parkinson's disease have shown the same effects of tolcapone on levodopa plasma concentrations that occur in healthy volunteers.

Pharmacokinetics of Tolcapone:

Tolcapone pharmacokinetics are linear over the dose range of 50 mg to 400 mg, independent of levodopa/carbidopa co-administration. The elimination half-life of tolcapone is 2 to 3 hours and there is no significant accumulation. With tid dosing of 100 mg or 200 mg, Cmax is approximately 3 mcg/mL and 6 mcg/mL, respectively.

Absorption:

Tolcapone is rapidly absorbed, with a Tmax of approximately 2 hours. The absolute bioavailability following oral administration is about 65%. Food given within 1 hour before and 2 hours after dosing of tolcapone decreases the relative bioavailability by 10% to 20% (see DOSAGE AND ADMINISTRATION).

Distribution:

The steady-state volume of distribution of tolcapone is small (9 L). Tolcapone does not distribute widely into tissues due to its high plasma protein binding. The plasma protein binding of tolcapone is >99.9% over the concentration range of 0.32 to 210 mcg/mL. In vitro experiments have shown that tolcapone binds mainly to serum albumin.

Metabolism and Elimination:

Tolcapone is almost completely metabolized prior to excretion, with only a very small amount (0.5% of dose) found unchanged in urine. The main metabolic pathway of tolcapone is glucuronidation; the glucuronide conjugate is inactive. In addition, the compound is methylated by COMT to 3-O-methyl-tolcapone. Tolcapone is metabolized to a primary alcohol (hydroxylation of the methyl group), which is subsequently oxidized to the carboxylic acid. In vitro experiments suggest that the oxidation may be catalyzed by cytochrome P450 3A4 and P450 2A6. The reduction to an amine and subsequent N-acetylation occur to a minor extent. After oral administration of a ^14C-labeled dose of tolcapone, 60% of labeled material is excreted in urine and 40% in feces. Tolcapone is a low-extraction-ratio drug (extraction ratio = 0.15) with a moderate systemic clearance of about 7 L/h.

Special Populations:

Tolcapone pharmacokinetics are independent of sex, age, body weight, and race (Japanese, Black and Caucasian). Polymorphic metabolism is unlikely based on the metabolic pathways involved.

Hepatic Impairment:

A study in patients with hepatic impairment has shown that moderate non-cirrhotic liver disease had no impact on the pharmacokinetics of tolcapone. In patients with moderate cirrhotic liver disease (Child-Pugh Class B), however, clearance and volume of distribution of unbound tolcapone was reduced by almost 50%. This reduction may increase the average concentration of unbound drug by twofold (see DOSAGE AND ADMINISTRATION). TASMAR therapy should not be initiated if the patient exhibits clinical evidence of active liver disease or two SGPT/ALT or SGOT/AST values greater than the upper limit of normal (see BOXED WARNING).

Renal Impairment:

The pharmacokinetics of tolcapone have not been investigated in a specific renal impairment study. However, the relationship of renal function and tolcapone pharmacokinetics has been investigated using population pharmacokinetics during clinical trials. The data of more than 400 patients have confirmed that over a wide range of creatinine clearance values (30 mL/min to 130 mL/min) the pharmacokinetics of tolcapone are unaffected by renal function. This could be explained by the fact that only a negligible amount of unchanged tolcapone (0.5%) is excreted in the urine. The glucuronide conjugate of tolcapone is mainly excreted in the urine but is also excreted in the bile. Accumulation of this stable and inactive metabolite should not present a risk in renally impaired patients with creatinine clearance above 25 mL/min (see DOSAGE AND ADMINISTRATION). Given the very high protein binding of tolcapone, no significant removal of the drug by hemodialysis would be expected.

Drug Interactions:

See PRECAUTIONS: Drug Interactions.

Clinical Studies:

The effectiveness of TASMAR as an adjunct to levodopa in the treatment of Parkinson's disease was established in three multicenter randomized controlled trials of 13 to 26 weeks' duration, supported by four 6-week trials whose results were consistent with those of the longer trials. In two of the longer trials, tolcapone was evaluated in patients whose Parkinson's disease was characterized by deterioration in their response to levodopa at the end of a dosing interval (so-called fluctuating patients with wearing-off phenomena). In the remaining trial, tolcapone was evaluated in patients whose response to levodopa was relatively stable (so-called non-fluctuators).

Fluctuating Patients:

In two 3-month trials, patients with documented episodes of wearing-off phenomena, despite optimum levodopa therapy, were randomized to receive placebo, tolcapone 100 mg tid or 200 mg tid. The formal double-blind portion of the trial was 3 months long, and the primary outcome was a comparison between treatments in the change from baseline in the amount of time spent "On" (a period of relatively good functioning) and "Off" (a period of relatively poor functioning). Patients recorded periodically, throughout the duration of the trial, the time spent in each of these states.

In addition to the primary outcome, patients were also assessed using sub-parts of the Unified Parkinson's Disease Rating Scale (UPDRS), a frequently used multi-item rating scale intended to evaluate mentation (Part I), activities of daily living (Part II), motor function (Part III), complications of therapy (Part IV), and disease staging (Parts V and VI); an Investigator's Global Assessment of Change (IGA), a subjective scale designed to assess global functioning in 5 areas of Parkinson's disease; the Sickness Impact Profile (SIP), a multi-item scale in 12 domains designed to assess the patient's functioning in multiple areas; and the change in daily levodopa/carbidopa dose.

In one of the studies, 202 patients were randomized in 11 centers in the United States and Canada. In this trial, all patients were receiving concomitant levodopa and carbidopa. In the second trial, 177 patients were randomized in 24 centers in Europe. In this trial, all patients were receiving concomitant levodopa and benserazide.

The following tables display the results of these 2 trials:

Table 1. U.S./Canadian Fluctuator Study
Primary Measure
 | Baseline (hrs) | Change from Baseline at Month 3 (hrs) | p-value [Compared to placebo. Nominal p values are not adjusted for multiple comparisons.]
Hours of Wake Time "Off" [Hours "Off" or "On" are based on the percent of waking day "Off" or "On", assuming a 16-hour waking day.]
Placebo | 6.2 | -1.2 | —
100 mg tid | 6.4 | -2.0 | 0.169
200 mg tid | 5.9 | -3.0 | <0.001
Hours of Wake Time "On"
Placebo | 8.7 | 1.4 | —
100 mg tid | 8.1 | 2.0 | 0.267
200 mg tid | 9.1 | 2.9 | 0.008
Secondary Measures
 | Baseline | Change from Baseline
 |  | at Month 3 | p-value
Levodopa Total Daily Dose (mg)
Placebo | 948 | 16 | —
100 mg tid | 788 | -166 | <0.001
200 mg tid | 865 | -207 | <0.001
Global (overall) % Improved
Placebo | — | 42 | —
100 mg tid | — | 71 | <0.001
200 mg tid | — | 91 | <0.001
UPDRS Motor
Placebo | 19.5 | -0.4 | —
100 mg tid | 17.6 | -1.9 | 0.217
200 mg tid | 20.6 | -2.0 | 0.210
UPDRS ADL
Placebo | 7.5 | -0.3 | —
100 mg tid | 7.7 | -0.8 | 0.487
200 mg tid | 8.3 | 0.2 | 0.412
SIP (total)
Placebo | 14.7 | -2.2 | —
100 mg tid | 14.9 | -0.4 | 0.210
200 mg tid | 17.6 | -0.3 | 0.216

Table 2. European Fluctuator Study
Primary Measure
 | Baseline (hrs) | Change from Baseline at Month 3 (hrs) | p-value [Compared to placebo. Nominal p values are not adjusted for multiple comparisons.]
Hours of Wake Time "Off" [Hours "Off" or "On" are based on the percent of waking day "Off" or "On", assuming a 16-hour waking day.]
Placebo | 6.1 | -0.7 | —
100 mg tid | 6.5 | -2.0 | 0.008
200 mg tid | 6.0 | -1.6 | 0.081
Hours of Wake Time "On"
Placebo | 8.5 | -0.1 | —
100 mg tid | 8.1 | 1.7 | 0.003
200 mg tid | 8.4 | 1.7 | 0.003
Secondary Measures
 | Baseline | Change from Baseline
 |  | at Month 3 | p-value
Levodopa Total Daily Dose (mg)
Placebo | 660 | -29 | —
100 mg tid | 667 | -109 | 0.025
200 mg tid | 675 | -122 | 0.010
Global (overall) % Improved
Placebo | — | 37 | —
100 mg tid | — | 70 | 0.003
200 mg tid | — | 78 | <0.001
UPDRS Motor
Placebo | 24.0 | -2.1 | —
100 mg tid | 22.4 | -4.2 | 0.163
200 mg tid | 22.4 | -6.5 | 0.004
UPDRS ADL
Placebo | 7.9 | -0.5 | —
100 mg tid | 7.5 | -0.9 | 0.408
200 mg tid | 7.7 | -1.3 | 0.097
SIP (total)
Placebo | 21.6 | -0.9 | —
100 mg tid | 16.6 | -1.9 | 0.419
200 mg tid | 18.4 | -4.2 | 0.011

Effects on “Off” time and levodopa dose did not differ by age or sex.

Non-fluctuating Patients:

In this study, 298 patients with idiopathic Parkinson's disease on stable doses of levodopa/carbidopa who were not experiencing wearing-off phenomena were randomized to placebo, tolcapone 100 mg tid, or tolcapone 200 mg tid for 6 months at 20 centers in the United States and Canada. The primary measure of effectiveness was the Activities of Daily Living portion (Subscale II) of the UPDRS. In addition, the change in daily levodopa dose, other subscales of the UPDRS, and the SIP were assessed as secondary measures. The results are displayed in the following table:

Table 3. U.S./Canadian Non-fluctuator Study
Primary Measure
 | Baseline | Change from Baseline
 |  | at Month 6 | p-value [Compared to placebo. Nominal p values are not adjusted for multiple comparisons.]
UPDRS ADL
Placebo | 8.5 | 0.1 | —
100 mg tid | 7.5 | -1.4 | <0.001
200 mg tid | 7.9 | -1.6 | <0.001
Secondary Measures
 | Baseline | Change from Baseline
 |  | at Month 6 | p-value
Levodopa Total Daily Dose (mg)
Placebo | 364 | 47 | —
100 mg tid | 370 | -21 | <0.001
200 mg tid | 381 | -32 | <0.001
UPDRS Motor
Placebo | 19.7 | 0.1 | —
100 mg tid | 17.3 | -2.0 | 0.018
200 mg tid | 16.0 | -2.3 | 0.008
SIP (total)
Placebo | 6.9 | 0.4 | —
100 mg tid | 7.3 | -0.9 | 0.044
200 mg tid | 7.3 | -0.7 | 0.078
Percent of Patients who
Developed Fluctuations
Placebo | — | 26 | —
100 mg tid | — | 19 | 0.297
200 mg tid | — | 14 | 0.047

Effects on Activities of Daily Living did not differ by age or sex.

INDICATIONS:

TASMAR is indicated as an adjunct to levodopa and carbidopa for the treatment of the signs and symptoms of idiopathic Parkinson's disease. Because of the risk of potentially fatal, acute fulminant liver failure, TASMAR (tolcapone) should ordinarily be used in patients with Parkinson's disease on l-dopa/carbidopa who are experiencing symptom fluctuations and are not responding satisfactorily to or are not appropriate candidates for other adjunctive therapies. Because of the risk of liver injury and because TASMAR, when it is effective, provides an observable symptomatic benefit, the patient who fails to show substantial clinical benefit within 3 weeks of initiation of treatment, should be withdrawn from TASMAR.

The effectiveness of TASMAR was demonstrated in randomized controlled trials in patients receiving concomitant levodopa therapy with carbidopa or another aromatic amino acid decarboxylase inhibitor who experienced end of dose wearing-off phenomena as well as in patients who did not experience such phenomena (see CLINICAL PHARMACOLOGY: Clinical Studies).

CONTRAINDICATIONS:

TASMAR tablets are contraindicated in patients with liver disease, in patients who were withdrawn from TASMAR because of evidence of TASMAR-induced hepatocellular injury or who have demonstrated hypersensitivity to the drug or its ingredients.

TASMAR is also contraindicated in patients with a history of nontraumatic rhabdomyolysis or hyperpyrexia and confusion possibly related to medication (see PRECAUTIONS: Events Reported With Dopaminergic Therapy).

WARNINGS:

(see BOXED WARNING) Because of the risk of potentially fatal, acute fulminant liver failure, TASMAR (tolcapone) should ordinarily be used in patients with Parkinson's disease on l-dopa/carbidopa who are experiencing symptom fluctuations and are not responding satisfactorily to or are not appropriate candidates for other adjunctive therapies (see INDICATIONS and DOSAGE AND ADMINISTRATION sections).

Because of the risk of liver injury and because TASMAR, when it is effective, provides an observable symptomatic benefit, the patient who fails to show substantial clinical benefit within 3 weeks of initiation of treatment, should be withdrawn from TASMAR.

TASMAR therapy should not be initiated if the patient exhibits clinical evidence of liver disease or two SGPT/ALT or SGOT/AST values greater than the upper limit of normal. Patients with severe dyskinesia or dystonia should be treated with caution (see PRECAUTIONS: Rhabdomyolysis).

Patients who develop evidence of hepatocellular injury while on TASMAR and are withdrawn from the drug for any reason may be at increased risk for liver injury if TASMAR is reintroduced. Accordingly, such patients should not ordinarily be considered for retreatment.

In controlled Phase 3 trials, increases to more than 3 times the upper limit of normal in ALT or AST occurred in approximately 1% of patients at 100 mg tid and 3% of patients at 200 mg tid. Females were more likely than males to have an increase in liver enzymes (approximately 5% vs 2%). Approximately one third of patients with elevated enzymes had diarrhea. Increases to more than 8 times the upper limit of normal in liver enzymes occurred in 0.3% at 100 mg tid and 0.7% at 200 mg tid. Elevated enzymes led to discontinuation in 0.3% and 1.7% of patients treated with 100 mg tid and 200 mg tid, respectively. Elevations usually occurred within 6 weeks to 6 months of starting treatment. In about half the cases with elevated liver enzymes, enzyme levels returned to baseline values within 1 to 3 months while patients continued TASMAR treatment. When treatment was discontinued, enzymes generally declined within 2 to 3 weeks but in some cases took as long as 1 to 2 months to return to normal.

Monoamine oxidase (MAO) and COMT are the two major enzyme systems involved in the metabolism of catecholamines. It is theoretically possible, therefore, that the combination of TASMAR and a non-selective MAO inhibitor (e.g., phenelzine and tranylcypromine) would result in inhibition of the majority of the pathways responsible for normal catecholamine metabolism. For this reason, patients should ordinarily not be treated concomitantly with TASMAR and a non-selective MAO inhibitor.

Tolcapone can be taken concomitantly with a selective MAO-B inhibitor (e.g., selegiline).

Falling Asleep During Activities of Daily Living and Somnolence

Tolcapone (TASMAR) increases plasma levels of levodopa in patients taking concomitant carbidopa levodopa products (see DOSAGE AND ADMINISTRATION). Patients taking carbidopa levodopa products alone or with other dopaminergic medications have reported suddenly falling asleep without prior warning of sleepiness while engaged in activities of daily living (includes the operation of motor vehicles). Some of these episodes resulted in automobile accidents. Although many of these patients reported somnolence while on TASMAR, some did perceive that they had no warning signs, such as excessive drowsiness, and believed that they were alert immediately prior to the event. Some patients reported these events one year after the initiation of treatment.

The risk for somnolence was increased with TASMAR treatment (TASMAR 100 mg-18%, 200 mg-14%, vs placebo-13%) compared to placebo treatment. In clinical trials, discontinuation due to somnolence occurred in 1% of patients treated with 200 mg TASMAR and 0% of patients treated with 100 mg TASMAR or placebo. Falling asleep while engaged in activities of daily living usually occurs in patients experiencing pre-existing somnolence, although some patients may not give such a history. For this reason, prescribers should continually reassess patients for drowsiness or sleepiness especially since some of the events occur well after the start of treatment. Prescribers should be aware that patients may not acknowledge drowsiness or sleepiness until directly questioned about drowsiness or sleepiness during specific activities. Patients who have already experienced somnolence or an episode of sudden sleep onset should not participate in these activities during treatment with TASMAR.

Before initiating treatment with TASMAR, advise patients about the potential to develop drowsiness and ask specifically about factors that may increase the risk for somnolence with TASMAR such as the use of concomitant sedating medications and the presence of sleep disorders. Consider discontinuing TASMAR in patients who report significant daytime sleepiness or episodes of falling asleep during activities that require active participation (e.g., conversations, eating, etc.). If treatment with TASMAR continues, patients should be advised not to drive and to avoid other potentially dangerous activities that might result in harm if patients become somnolent. There is insufficient information to establish that dose reduction will eliminate episodes of falling asleep while engaged in activities of daily living.

PRECAUTIONS:

Hypotension/Syncope:

Dopaminergic therapy in Parkinson's disease patients has been associated with orthostatic hypotension. Tolcapone enhances levodopa bioavailability and, therefore, may increase the occurrence of orthostatic hypotension. In TASMAR clinical trials, orthostatic hypotension was documented at least once in 8%, 14% and 13% of the patients treated with placebo, 100 mg and 200 mg TASMAR tid, respectively. A total of 2%, 5% and 4% of the patients treated with placebo, 100 mg and 200 mg TASMAR tid, respectively, reported orthostatic symptoms at some time during their treatment and also had at least one episode of orthostatic hypotension documented (however, the episode of orthostatic symptoms itself was invariably not accompanied by vital sign measurements). Patients with orthostasis at baseline were more likely than patients without symptoms to have orthostatic hypotension during the study, irrespective of treatment group. In addition, the effect was greater in tolcapone-treated patients than in placebo-treated patients. Baseline treatment with dopamine agonists or selegiline did not appear to increase the likelihood of experiencing orthostatic hypotension when treated with TASMAR. Approximately 0.7% of the patients treated with TASMAR (5% of patients who were documented to have had at least one episode of orthostatic hypotension) eventually withdrew from treatment due to adverse events presumably related to hypotension.

In controlled Phase 3 trials, approximately 5%, 4% and 3% of tolcapone 200 mg tid, 100 mg tid and placebo patients, respectively, reported at least one episode of syncope. Reports of syncope were generally more frequent in patients in all three treatment groups who had an episode of documented hypotension (although the episodes of syncope, obtained by history, were themselves not documented with vital sign measurement) compared to patients who did not have any episodes of documented hypotension.

Diarrhea:

In clinical trials, diarrhea developed in approximately 8%, 16% and 18% of patients treated with placebo, 100 mg and 200 mg TASMAR tid, respectively. While diarrhea was generally regarded as mild to moderate in severity, approximately 3% to 4% of patients on tolcapone had diarrhea which was regarded as severe. Diarrhea was the adverse event which most commonly led to discontinuation, with approximately 1%, 5% and 6% of patients treated with placebo, 100 mg and 200 mg TASMAR tid, respectively, withdrawing from the trials prematurely. Discontinuing TASMAR for diarrhea was related to the severity of the symptom. Diarrhea resulted in withdrawal in approximately 8%, 40% and 70% of patients with mild, moderate and severe diarrhea, respectively. Although diarrhea generally resolved after discontinuation of TASMAR, it led to hospitalization in 0.3%, 0.7% and 1.7% of patients in the placebo, 100 mg and 200 mg TASMAR tid groups.

Typically, diarrhea presents 6 to 12 weeks after tolcapone is started, but it may appear as early as 2 weeks and as late as many months after the initiation of treatment. Clinical trial data suggested that diarrhea associated with tolcapone use may sometimes be associated with anorexia (decreased appetite).

No consistent description of tolcapone-induced diarrhea has been derived from clinical trial data, and the mechanism of action is currently unknown.

It is recommended that all cases of persistent diarrhea should be followed up with an appropriate work-up (including occult blood samples).

Hallucinations/Psychotic-Like Behavior:

In clinical trials, hallucinations developed in approximately 5% of patients treated with placebo, compared to 8% and 10% of patients treated with 100 mg or 200 mg three times per day, respectively. Hallucinations led to drug discontinuation and premature withdrawal from clinical trials in 0.3% of patients treated with placebo, compared to 1.4% and 1.0% of patients treated with TASMAR 100 mg or 200 mg TASMAR three times per day, respectively. Hallucinations led to hospitalization in 0.0% of patients in the placebo group, compared to 1.7% and 0.0% of patients treated with 100 mg or 200 mg TASMAR three times per day, respectively.

In general, hallucinations present shortly after the initiation of therapy with tolcapone (typically within the first 2 weeks). Clinical trial data suggest that hallucinations associated with tolcapone use may be responsive to levodopa dose reduction. Patients whose hallucinations resolved had a mean levodopa dose reduction of 175 mg to 200 mg (20% to 25%) after the onset of the hallucinations. Hallucinations were commonly accompanied by confusion and to a lesser extent sleep disorder (insomnia) and excessive dreaming. The incidence of hallucination may be increased in elderly patients over 75 years treated with TASMAR (see Geriatric Use).

Postmarketing reports indicate that patients may experience new or worsening mental status and behavioral changes, which may be severe, including psychotic-like behavior during TASMAR treatment or after starting or increasing the dose of TASMAR. Other drugs prescribed to improve the symptoms of Parkinson’s disease may have similar effects on thinking and behavior. This abnormal thinking and behavior may present with one or more symptoms, including paranoid ideation, delusions, hallucinations, confusion, psychotic-like behavior, disorientation, aggressive behavior, agitation, and delirium.

Ordinarily, patients with a major psychotic disorder should not be treated with TASMAR because of the risk of exacerbating psychosis. In addition, certain medications used to treat psychosis may exacerbate the symptoms of Parkinson's disease and may decrease the effectiveness of TASMAR.

Dyskinesia:

TASMAR may potentiate the dopaminergic side effects of levodopa and may cause and/or exacerbate preexisting dyskinesia. Although decreasing the dose of levodopa may ameliorate this side effect, many patients in controlled trials continued to experience frequent dyskinesias despite a reduction in their dose of levodopa. Dyskinesia was the most common adverse reaction observed in controlled trials and developed in approximately 20% of patients treated with placebo, compared to 42% and 51% of patients treated with TASMAR 100 mg or 200 mg three times daily, respectively. The rates of withdrawal for dyskinesia were 0.0% in the placebo group, compared to 0.3% and 1.0% in the groups receiving TASMAR 100 mg or 200 mg three times a day, respectively.

Impulse Control/Compulsive Behaviors:

Reports suggest that patients may experience an intense urge to gamble, increased sexual urges, intense urges to spend money, binge eating, and/or other intense urges, and the inability to control these urges. These reports are associated with patients taking TASMAR in conjunction with carbidopa/levodopa, as well as other medications that increase central dopaminergic tone and that are used to treat patients with Parkinson’s disease. In some cases, although not all, these urges were reported to have stopped when the dose was reduced or the medication was discontinued. Because patients may not recognize these behaviors as abnormal, it is important for prescribers to specifically ask patients or their caregivers about the development of new or increased gambling urges, sexual urges, uncontrolled spending or other urges while being treated with TASMAR. Physicians should consider dose reduction or stopping the medication if a patient develops such urges while taking TASMAR (see Information for Patients).

Rhabdomyolysis:

Cases of severe rhabdomyolysis, with one case of multi-organ system failure rapidly progressing to death, have been reported. The complicated nature of these cases makes it impossible to determine what role, if any, TASMAR played in their pathogenesis. Severe prolonged motor activity including dyskinesia may account for rhabdomyolysis. Some cases, however, included fever, alteration of consciousness and muscular rigidity. It is possible, therefore, that the rhabdomyolysis may be a result of the syndrome described in Hyperpyrexia and Confusion (see PRECAUTIONS: Events Reported With Dopaminergic Therapy).

Renal Impairment:

No dosage adjustment is needed in patients with mild to moderate renal impairment, however, patients with severe renal impairment should be treated with caution (see CLINICAL PHARMACOLOGY: Pharmacokinetics of Tolcapone and DOSAGE AND ADMINISTRATION).

Renal Toxicity:

When rats were dosed daily for 1 or 2 years (exposures 6 times the human exposure or greater) there was a high incidence of proximal tubule cell damage consisting of degeneration, single cell necrosis, hyperplasia, karyocytomegaly and atypical nuclei. These effects were not associated with changes in clinical chemistry parameters, and there is no established method for monitoring for the possible occurrence of these lesions in humans. Although it has been speculated that these toxicities may occur as the result of a species-specific mechanism, experiments that would confirm the theory have not been conducted.

Hepatic Impairment:

Because of the risk of liver injury, TASMAR therapy should not be initiated in any patient with liver disease. For similar reasons, treatment should not be initiated in patients who have two SGPT/ALT or SGOT/AST values greater than the upper limit of normal (see BOXED WARNING) or any other evidence of hepatocellular dysfunction.

Hematuria:

The rates of hematuria in placebo-controlled trials were approximately 2%, 4% and 5% in placebo, 100 mg and 200 mg TASMAR tid, respectively. The etiology of the increase with TASMAR has not always been explained (for example, by urinary tract infection or warfarin therapy). In placebo-controlled trials in the United States (N=593) rates of microscopically confirmed hematuria were approximately 3%, 2% and 2% in placebo, 100 mg and 200 mg TASMAR tid, respectively.

Events Reported With Dopaminergic Therapy:

The events listed below are known to be associated with the use of drugs that increase dopaminergic activity, although they are most often associated with the use of direct dopamine agonists. While cases of Hyperpyrexia and Confusion have been reported in association with tolcapone withdrawal (see paragraph below), the expected incidence of fibrotic complications is so low that even if tolcapone caused these complications at rates similar to those attributable to other dopaminergic therapies, it is unlikely that even a single example would have been detected in a cohort of the size exposed to tolcapone.

Hyperpyrexia and Confusion:

In clinical trials, four cases of a symptom complex resembling the neuroleptic malignant syndrome (characterized by elevated temperature, muscular rigidity, and altered consciousness), similar to that reported in association with the rapid dose reduction or withdrawal of other dopaminergic drugs, have been reported in association with the abrupt withdrawal or lowering of the dose of tolcapone. In three of these cases, CPK was elevated as well. One patient died, and the other three patients recovered over periods of approximately 2, 4 and 6 weeks. Rare cases of this symptom complex have been reported during marketed use. It is difficult to determine if TASMAR played a role in the pathogenesis of these events because these patients received several concomitant medications affecting the central nervous system such as monoaminergic (i.e., MAO-I, tricyclic and selective serotonin reuptake inhibitors) and anticholinergic agents.

Fibrotic Complications:

Cases of retroperitoneal fibrosis, pulmonary infiltrates, pleural effusion, and pleural thickening have been reported in some patients treated with ergot derived dopaminergic agents. While these complications may resolve when the drug is discontinued, complete resolution does not always occur. Although these adverse events are believed to be related to the ergoline structure of these compounds, whether other, nonergot derived drugs (e.g., tolcapone) that increase dopaminergic activity can cause them is unknown.

Three cases of pleural effusion, one with pulmonary fibrosis, occurred during clinical trials. These patients were also on concomitant dopamine agonists (pergolide or bromocriptine) and had a prior history of cardiac disease or pulmonary pathology (nonmalignant lung lesion).

Melanoma:

Epidemiological studies have shown that patients with Parkinson's disease have a higher risk (2- to approximately 6-fold higher) of developing melanoma than the general population. Whether the increased risk observed was due to Parkinson's disease or other factors, such as drugs used to treat Parkinson's disease, is unclear.

For the reasons stated above, patients and providers are advised to monitor for melanomas frequently and on a regular basis when using TASMAR for any indication. Ideally, periodic skin examination should be performed by appropriately qualified individuals (e.g., dermatologists).

Information for Patients:

Patients should be instructed to take TASMAR only as prescribed.

TASMAR should not be used by patients until there has been a complete discussion of the risks and the patient has provided written acknowledgement that the risks have been explained (see PATIENT ACKNOWLEDGEMENT OF RISKSsection).

Inform patients about clinical signs and symptoms that suggest the onset of hepatic injury (persistent nausea, fatigue, lethargy, anorexia, jaundice, dark urine, pruritus, and right upper quadrant tenderness) (see WARNINGS). If symptoms of hepatic failure occur, patients should be advised to contact their physician immediately.

Inform patients of the need to have regular blood tests to monitor liver enzymes.

Advise patients that sleepiness or drowsiness may occur and that they should not drive a car or operate other complex machinery until they have gained sufficient experience on TASMAR to gauge whether or not it adversely affects their mental and/or motor performance. Advise patients to exercise caution while driving, operating machines, or working at heights during treatment with TASMAR. Because of the possible additive sedative effects, caution should also be used when patients are taking other CNS depressants in combination with TASMAR. Inform patients that nausea may occur, especially at the initiation of treatment with TASMAR.

Inform patients that hallucinations and other psychotic-like behavior may occur.

Advise patients about the possibility of developing or worsening of existing dyskinesia and/or dystonia after starting TASMAR.

Advise patients that they may develop postural (orthostatic) hypotension with or without symptoms such as dizziness, nausea, syncope, and sometimes sweating. Advise patients to rise slowly, especially after long periods of sitting or lying down. Hypotension may be more likely when patients first start treatment with TASMAR.

Instruct patients and caregivers to report intense urges to gamble, increased sexual urges, increase in spending money, binge eating, and other intense urges as well as the inability to control these urges to the prescriber while taking TASMAR.

Although TASMAR has not been shown to be teratogenic in animals, it is always given in conjunction with levodopa/carbidopa, which is known to cause visceral and skeletal malformations in the rabbit. Accordingly, patients should be advised to notify their physicians if they become pregnant or intend to become pregnant during therapy (see PRECAUTIONS: Pregnancy).

Tolcapone is excreted into maternal milk in rats. Because of the possibility that tolcapone may be excreted into human milk, advise patients to notify their physicians if they intend to breastfeed or are breastfeeding an infant.

Laboratory Tests:

Although a program of frequent laboratory monitoring for evidence of hepatocellular injury is deemed essential, it is not clear that periodic monitoring of liver enzymes will prevent the occurrence of fulminant liver failure. However, it is generally believed that early detection of drug-induced hepatic injury along with immediate withdrawal of the suspect drug enhances the likelihood for recovery. Accordingly, the following liver monitoring program is recommended.

Before starting treatment with TASMAR, the physician should conduct appropriate tests to exclude the presence of liver disease. In patients determined to be appropriate candidates for treatment with TASMAR, serum glutamic-pyruvic transaminase (SGPT/ALT) and serum glutamic-oxaloacetic transaminase (SGOT/AST) levels should be determined at baseline and periodically (i.e. every 2 to 4 weeks) for the first 6 months of therapy. After the first six months, periodic monitoring is recommended at intervals deemed clinically relevant. Although more frequent monitoring increases the chances of early detection, the precise schedule for monitoring is a matter of clinical judgment.

If the dose is increased to 200 mg tid (see DOSAGE AND ADMINISTRATION), liver enzyme monitoring should take place before increasing the dose and then be conducted every 2 to 4 weeks for the following 6 months of therapy. After six months, periodic monitoring is recommended at intervals deemed clinically relevant.

Discontinue TASMAR if SGPT/ALT or SGOT/AST levels exceed 2 times the upper limit of normal or if clinical signs and symptoms suggest the onset of hepatic dysfunction (e.g., persistent nausea, fatigue, lethargy, anorexia, jaundice, dark urine, pruritus, and right upper quadrant tenderness).

Special Populations:

TASMAR therapy should not be initiated if the patient exhibits clinical evidence of active liver disease or two SGPT/ALT or SGOT/AST values greater than the upper limit of normal. Patients with severe dyskinesia or dystonia should be treated with caution (see PRECAUTIONS: Rhabdomyolysis). Patients with severe renal impairment should be treated with caution (see INDICATIONS, DOSAGE AND ADMINISTRATION, BOXED WARNING and WARNINGS).

Drug Interactions:

Protein Binding:

Although tolcapone is highly protein bound, in vitro studies have shown that tolcapone at a concentration of 50 mcg/mL did not displace other highly protein-bound drugs from their binding sites at therapeutic concentrations. The experiments included warfarin (0.5 to 7.2 mcg/mL), phenytoin (4.0 to 38.7 mcg/mL), tolbutamide (24.5 to 96.1 mcg/mL) and digitoxin (9.0 to 27.0 mcg/mL).

Drugs Metabolized by Catechol-O-Methyltransferase (COMT):

Tolcapone may influence the pharmacokinetics of drugs metabolized by COMT. However, no effects were seen on the pharmacokinetics of the COMT substrate carbidopa. The effect of tolcapone on the pharmacokinetics of other drugs of this class such as α-methyldopa, dobutamine, apomorphine, and isoproterenol has not been evaluated. A dose reduction of such compounds should be considered when they are co-administered with tolcapone.

Effect of Tolcapone on the Metabolism of Other Drugs:

In vitro experiments have been performed to assess the potential of tolcapone to interact with isoenzymes of cytochrome P450 (CYP). No relevant interactions with substrates for CYP 2A6 (warfarin), CYP 1A2 (caffeine), CYP 3A4 (midazolam, terfenadine, cyclosporine), CYP 2C19 (S-mephenytoin) and CYP 2D6 (desipramine) were observed in vitro. The absence of an interaction with desipramine, a drug metabolized by cytochrome P450 2D6, was also confirmed in an in vivo study where tolcapone did not change the pharmacokinetics of desipramine.

Due to its affinity to cytochrome P450 2C9 in vitro, tolcapone may interfere with drugs, whose clearance is dependent on this metabolic pathway, such as tolbutamide and warfarin. However, in an in vivo interaction study, tolcapone did not change the pharmacokinetics of tolbutamide. Therefore, clinically relevant interactions involving cytochrome P450 2C9 appear unlikely. Similarly, tolcapone did not affect the pharmacokinetics of desipramine, a drug metabolized by cytochrome P450 2D6, indicating that interactions with drugs metabolized by that enzyme are unlikely. Since clinical information is limited regarding the combination of warfarin and tolcapone, coagulation parameters should be monitored when these two drugs are co-administered.

Drugs That Increase Catecholamines:

Tolcapone did not influence the effect of ephedrine, an indirect sympathomimetic, on hemodynamic parameters or plasma catecholamine levels, either at rest or during exercise. Since tolcapone did not alter the tolerability of ephedrine, these drugs can be co-administered.

When TASMAR was given together with levodopa/carbidopa and desipramine, there was no significant change in blood pressure, pulse rate and plasma concentrations of desipramine. Overall, the frequency of adverse events increased slightly. These adverse events were predictable based on the known adverse reactions to each of the three drugs individually. Therefore, caution should be exercised when desipramine is administered to Parkinson's disease patients being treated with TASMAR and levodopa/carbidopa.

In clinical trials, patients receiving TASMAR/levodopa preparations reported a similar adverse event profile independent of whether or not they were also concomitantly administered selegiline (a selective MAO-B inhibitor).

Carcinogenesis, Mutagenesis and Impairment of Fertility:

Carcinogenesis:

Carcinogenicity studies in which tolcapone was administered in the diet were conducted in mice and rats. Mice were treated for 80 (female) or 95 (male) weeks with doses of 100, 300 and 800 mg/kg/day, equivalent to 0.8, 1.6 and 4 times human exposure (AUC = 80 mcg∙hr/mL) at the recommended daily clinical dose of 600 mg. Rats were treated for 104 weeks with doses of 50, 250 and 450 mg/kg/day. Tolcapone exposures were 1, 6.3 and 13 times the human exposure in male rats and 1.7, 11.8 and 26.4 times the human exposure in female rats. There was an increased incidence of uterine adenocarcinomas in female rats at exposure equivalent to 26.4 times the human exposure. There was evidence of renal tubular injury and renal tubular tumor formation in rats. A low incidence of renal tubular cell adenomas occurred in middle- and high-dose female rats; tubular cell carcinomas occurred in middle- and high-dose male and high-dose female rats, with a statistically significant increase in high-dose males. Exposures were equivalent to 6.3 (males) or 11.8 (females) times the human exposure or greater; no renal tumors were observed at exposures of 1 (males) or 1.7 (females) times the human exposure. Minimal-to-marked damage to the renal tubules, consisting of proximal tubule cell degeneration, single cell necrosis, hyperplasia and karyocytomegaly, occurred at the doses associated with renal tumors. Renal tubule damage, characterized by proximal tubule cell degeneration and the presence of atypical nuclei, as well as one adenocarcinoma in a high-dose male, were observed in a 1-year study in rats receiving doses of tolcapone of 150 and 450 mg/kg/day. These histopathological changes suggest the possibility that renal tumor formation might be secondary to chronic cell damage and sustained repair, but this relationship has not been established, and the relevance of these findings to humans is not known. There was no evidence of carcinogenic effects in the long-term mouse study. The carcinogenic potential of tolcapone in combination with levodopa/carbidopa has not been examined.

Mutagenesis:

Tolcapone was clastogenic in the in vitro mouse lymphoma/thymidine kinase assay in the presence of metabolic activation. Tolcapone was not mutagenic in the Ames test, the in vitro V79/HPRT gene mutation assay, or the unscheduled DNA synthesis assay. It was not clastogenic in an in vitro chromosomal aberration assay in cultured human lymphocytes, or in an in vivo micronucleus assay in mice.

Impairment of Fertility:

Tolcapone did not affect fertility and general reproductive performance in rats at doses up to 300 mg/kg/day (5.7 times the human dose on a mg/m^2 basis).

Pregnancy:

Tolcapone, when administered alone during organogenesis, was not teratogenic at doses of up to 300 mg/kg/day in rats or up to 400 mg/kg/day in rabbits (5.7 times and 15 times the recommended daily clinical dose of 600 mg, on a mg/m^2 basis, respectively). In rabbits, however, an increased rate of abortion occurred at a dose of 100 mg/kg/day (3.7 times the daily clinical dose on a mg/m^2 basis) or greater. Evidence of maternal toxicity (decreased weight gain, death) was observed at 300 mg/kg in rats and 400 mg/kg in rabbits. When tolcapone was administered to female rats during the last part of gestation and throughout lactation, decreased litter size and impaired growth and learning performance in female pups were observed at a dose of 250/150 mg/kg/day (dose reduced from 250 to 150 mg/kg/day during late gestation due to high rate of maternal mortality; equivalent to 4.8/2.9 times the clinical dose on a mg/m^2 basis).

Tolcapone is always given concomitantly with levodopa/carbidopa, which is known to cause visceral and skeletal malformations in rabbits. The combination of tolcapone (100 mg/kg/day) with levodopa/carbidopa (80/20 mg/kg/day) produced an increased incidence of fetal malformations (primarily external and skeletal digit defects) compared to levodopa/carbidopa alone when pregnant rabbits were treated throughout organogenesis. Plasma exposures to tolcapone (based on AUC) were 0.5 times the expected human exposure, and plasma exposures to levodopa were 6 times higher than those in humans under therapeutic conditions. In a combination embryo-fetal development study in rats, fetal body weights were reduced by the combination of tolcapone (10, 30 and 50 mg/kg/day) and levodopa/carbidopa (120/30 mg/kg/day) and by levodopa/carbidopa alone. Tolcapone exposures were 0.5 times expected human exposure or greater: levodopa exposures were 21 times the expected human exposure or greater. The high dose of 50 mg/kg/day of tolcapone given alone was not associated with reduced fetal body weight (plasma exposures of 1.4 times the expected human exposure).

There is no experience from clinical studies regarding the use of TASMAR in pregnant women. Therefore, TASMAR should be used during pregnancy only if the potential benefit justifies the potential risk to the fetus.

Nursing Women:

In animal studies, tolcapone was excreted into maternal rat milk.

It is not known whether tolcapone is excreted in human milk. Because many drugs are excreted in human milk, caution should be exercised when tolcapone is administered to a nursing woman.

Pediatric Use:

There is no identified potential use of tolcapone in pediatric patients.

Geriatric Use:

Parkinson’s disease is primarily an affliction of the elderly. Consequently, the mean age of patients in tolcapone clinical trials was 60 to 65 years. To investigate safety as it relates to advancing age, three subgroups were identified: less than 65 years, 65 to 75 years, and greater than 75 years. There were generally no consistent age-related trends in safety parameters. However, patients greater than 75 years of age may be more likely to develop hallucinations than patients less than 75 years of age, while patients over 75 may be less likely to develop dystonia (see PRECAUTIONS: Hallucinations/Psychotic-Like Behavior). In tolcapone clinical trials, measures of therapeutic efficacy (effects on “Off” time, levodopa dose, and effects on Activities of Daily Living) were not affected by age (see CLINICAL PHARMACOLOGY: Clinical Studies). Tolcapone pharmacokinetics have not been found to be affected by age (see CLINICAL PHARMACOLOGY: Special Populations).

ADVERSE REACTIONS:

Cases of severe hepatocellular injury, including fulminant liver failure resulting in death, have been reported in postmarketing use. As of May 2005, three cases of fatal fulminant hepatic failure have been reported from more than 40,000 patient years of worldwide use. This incidence may be 10- to 100-fold higher than the background incidence in the general population. All three cases were reported within the first six months of initiation of treatment with TASMAR. Analysis of the laboratory monitoring data in over 3,400 TASMAR-treated patients participating in clinical trials indicated that increases in SGPT/ALT or SGOT/AST, when present, generally occurred within the first 6 months of treatment with TASMAR.

The imprecision of the estimated increase is due to uncertainties about the base rate and the actual number of cases occurring in association with TASMAR. The incidence of idiopathic potentially fatal fulminant hepatic failure (i.e., not due to viral hepatitis or alcohol) is low. One estimate, based upon transplant registry data, is approximately 3/1,000,000 patients per year in the United States. Whether this estimate is an appropriate basis for estimating the increased risk of liver failure among TASMAR users is uncertain. TASMAR users, for example, differ in age and general health status from candidates for liver transplantation. Similarly, underreporting of cases may lead to significant underestimation of the increased risk associated with the use of TASMAR.

During the premarketing development of tolcapone, two distinct patient populations were studied, patients with end-of-dose wearing-off phenomena and patients with stable responses to levodopa therapy. All patients received concomitant treatment with levodopa preparations, however, and were similar in other clinical aspects. Adverse reactions are shown for these two populations combined.

The most commonly observed adverse reactions in the double-blind, placebo-controlled trials (N=892), with a difference in incidence (TASMAR minus Placebo) of at least 5% or greater in the 100 mg or 200 mg TASMAR-treated groups compared to placebo, were dyskinesia, nausea, diarrhea, anorexia, sleep disorder, vomiting, urine discoloration, somnolence, hallucination, dystonia, and sweating.

Approximately 16% of the 592 patients who participated in the double-blind, placebo-controlled trials discontinued treatment due to adverse reactions compared to 10% of the 298 patients who received placebo. Diarrhea was by far the most frequent cause of discontinuation (approximately 6% in tolcapone patients vs. 1% on placebo).

Adverse Reaction Incidence in Controlled Clinical Studies:

Table 4 lists treatment emergent adverse reactions that occurred in at least 1% of patients treated with tolcapone participating in the double-blind, placebo-controlled studies and were numerically more common in at least one of the tolcapone groups. In these studies, either tolcapone or placebo was added to levodopa/carbidopa (or benserazide).

The prescriber should be aware that these figures cannot be used to predict the incidence of adverse reactions in the course of usual medical practice where patient characteristics and other factors differ from those that prevailed in the clinical studies. Similarly, the cited frequencies cannot be compared with figures obtained from other clinical investigations involving different treatments, uses, and investigators. However, the cited figures do provide the prescriber with some basis for estimating the relative contribution of drug and nondrug factors to the adverse reactions incidence rate in the population studied.

Table 4. Summary of Patients With Adverse Reactions After Start of Trial Drug Administration (At Least 1% in TASMAR Group and at Least One TASMAR Dose Group Greater Than Placebo)
 | Placebo | Tolcapone tid
 |  | 100 mg | 200 mg
 | N = 298 | N = 296 | N = 298
Adverse Reactions | (%) | (%) | (%)
Dyskinesia | 20 | 42 | 51
Nausea | 18 | 30 | 35
Sleep Disorder | 18 | 24 | 25
Dystonia | 17 | 19 | 22
Dreaming Excessive | 17 | 21 | 16
Anorexia | 13 | 19 | 23
Cramps Muscle | 17 | 17 | 18
Orthostatic Complaints | 14 | 17 | 17
Somnolence | 13 | 18 | 14
Diarrhea | 8 | 16 | 18
Confusion | 9 | 11 | 10
Dizziness | 10 | 13 | 6
Headache | 7 | 10 | 11
Hallucination | 5 | 8 | 10
Vomiting | 4 | 8 | 10
Constipation | 5 | 6 | 8
Fatigue | 6 | 7 | 3
Upper Respiratory Tract Infection | 3 | 5 | 7
Falling | 4 | 4 | 6
Sweating Increased | 2 | 4 | 7
Urinary Tract Infection | 4 | 5 | 5
Xerostomia | 2 | 5 | 6
Abdominal Pain | 3 | 5 | 6
Syncope | 3 | 4 | 5
Urine Discoloration | 1 | 2 | 7
Dyspepsia | 2 | 4 | 3
Influenza | 2 | 3 | 4
Dyspnea | 2 | 3 | 3
Balance Loss | 2 | 3 | 2
Flatulence | 2 | 2 | 4
Hyperkinesia | 1 | 3 | 2
Chest Pain | 1 | 3 | 1
Hypotension | 1 | 2 | 2
Paresthesia | 2 | 3 | 1
Stiffness | 1 | 2 | 2
Arthritis | 1 | 2 | 1
Chest Discomfort | 1 | 1 | 2
Hypokinesia | 1 | 1 | 3
Micturition Disorder | 1 | 2 | 1
Pain Neck | 1 | 2 | 2
Burning | 0 | 2 | 1
Sinus Congestion | 0 | 2 | 1
Agitation | 0 | 1 | 1
Bleeding Dermal | 0 | 1 | 1
Irritability | 0 | 1 | 1
Mental Deficiency | 0 | 1 | 1
Hyperactivity | 0 | 1 | 1
Malaise | 0 | 1 | 0
Panic Reaction | 0 | 1 | 0
Tumor Skin | 0 | 1 | 0
Cataract | 0 | 1 | 0
Euphoria | 0 | 1 | 0
Fever | 0 | 0 | 1
Alopecia | 0 | 1 | 0
Eye Inflamed | 0 | 1 | 0
Hypertonia | 0 | 0 | 1
Tumor Uterus | 0 | 1 | 0

Effects of Gender on Adverse Reactions:

Female patients may be more likely to develop somnolence than males.

Other Adverse Events Observed During All Trials in Patients With Parkinson's Disease:

During these trials, all adverse events were recorded by the clinical investigators using terminology of their own choosing. To provide a meaningful estimate of the proportion of individuals having adverse events, similar types of adverse events were grouped into a smaller number of standardized categories using COSTART dictionary terminology. These categories are used in the listing below.

All reported events that occurred at least twice (or once for serious or potentially serious events), except those already listed above, trivial events and terms too vague to be meaningful are included, without regard to determination of a causal relationship to TASMAR.

Events are further classified within body system categories and enumerated in order of decreasing frequency using the following definitions: frequent adverse events are defined as those occurring in at least 1/100 patients; infrequent adverse events are defined as those occurring in between 1/100 and 1/1000 patients; and rare adverse events are defined as those occurring in fewer than 1/1000 patients.

Nervous System — frequent: depression, hypesthesia, tremor, speech disorder, vertigo, emotional lability; infrequent: neuralgia, amnesia, extrapyramidal syndrome, hostility, libido increased, manic reaction, nervousness, paranoid reaction, cerebral ischemia, cerebrovascular accident, delusions, libido decreased, neuropathy, apathy, choreoathetosis, myoclonus, psychosis, thinking abnormal, twitching; rare: antisocial reaction, delirium, encephalopathy, hemiplegia, meningitis.

Digestive System — frequent: tooth disorder; infrequent: dysphagia, gastrointestinal hemorrhage, gastroenteritis, mouth ulceration, increased salivation, abnormal stools, esophagitis, cholelithiasis, colitis, tongue disorder, rectal disorder; rare: cholecystitis, duodenal ulcer, gastrointestinal carcinoma, stomach atony.

Body as a Whole — frequent: flank pain, accidental injury, abdominal pain, infection; infrequent: hernia, pain, allergic reaction, cellulitis, infection fungal, viral infection, carcinoma, chills, infection bacterial, neoplasm, abscess, face edema; rare: death.

Cardiovascular System — frequent: palpitation; infrequent: hypertension, vasodilation, angina pectoris, heart failure, atrial fibrillation, tachycardia, migraine, aortic stenosis, arrhythmia, arteriospasm, bradycardia, cerebral hemorrhage, coronary artery disorder, heart arrest, myocardial infarct, myocardial ischemia, pulmonary embolus; rare: arteriosclerosis, cardiovascular disorder, pericardial effusion, thrombosis.

Musculoskeletal System — frequent: myalgia; infrequent: tenosynovitis, arthrosis, joint disorder.

Urogenital System — frequent: urinary incontinence, impotence; infrequent: prostatic disorder, dysuria, nocturia, polyuria, urinary retention, urinary tract disorder, hematuria, kidney calculus, prostatic carcinoma, breast neoplasm, oliguria, uterine atony, uterine disorder, vaginitis; rare: bladder calculus, ovarian carcinoma, uterine hemorrhage.

Respiratory System — frequent: bronchitis, pharyngitis; infrequent: cough increased, rhinitis, asthma, epistaxis, hyperventilation, laryngitis, hiccup; rare: apnea, hypoxia, lung edema.

Skin and Appendages — frequent: rash; infrequent: herpes zoster, pruritus, seborrhea, skin discoloration, eczema, erythema multiforme, skin disorder, furunculosis, herpes simplex, urticaria.

Special Senses — frequent: tinnitus; infrequent: diplopia, ear pain, eye hemorrhage, eye pain, lacrimation disorder, otitis media, parosmia; rare: glaucoma.

Metabolic and Nutritional — infrequent: edema, hypercholesteremia, thirst, dehydration.

Hemic and Lymphatic System — infrequent: anemia; rare: leukemia, thrombocytopenia.

Endocrine System — infrequent: diabetes mellitus.

Unclassified — infrequent: surgical procedure.

To report SUSPECTED ADVERSE REACTIONS, contact Bausch Health US, LLC at 1-800-321-4576 or FDA at 1-800-FDA-1088 or www.fda.gov/medwatch.

DRUG ABUSE AND DEPENDENCE:

Tolcapone is not a controlled substance.

Studies conducted in rats and monkeys did not reveal any potential for physical or psychological dependence. Although clinical trials have not revealed any evidence of the potential for abuse, tolerance or physical dependence, systematic studies in humans designed to evaluate these effects have not been performed.

OVERDOSAGE:

The highest dose of tolcapone administered to humans was 800 mg tid, with and without levodopa/carbidopa co-administration. This was in a 1-week study in elderly, healthy volunteers. The peak plasma concentrations of tolcapone at this dose were on average 30 mcg/mL (compared to 3 mcg/mL and 6 mcg/mL with 100 mg and 200 mg tolcapone, respectively). Nausea, vomiting and dizziness were observed, particularly in combination with levodopa/carbidopa.

The threshold for the lethal plasma concentration for tolcapone based on animal data is >100 mcg/mL. Respiratory difficulties were observed in rats at high oral (gavage) and intravenous doses and in dogs with rapidly injected intravenous doses.

Management of Overdose:

Hospitalization is advised. General supportive care is indicated. Based on the physicochemical properties of the compound, hemodialysis is unlikely to be of benefit.

DOSAGE AND ADMINISTRATION:

Because of the risk of potentially fatal, acute fulminant liver failure, TASMAR (tolcapone) should ordinarily be used in patients with Parkinson's disease on l-dopa/carbidopa who are experiencing symptom fluctuations and are not responding satisfactorily to or are not appropriate candidates for other adjunctive therapies (see INDICATIONS and DOSAGE AND ADMINISTRATION sections).

BECAUSE OF THE RISK OF LIVER INJURY AND BECAUSE TASMAR WHEN IT IS EFFECTIVE PROVIDES AN OBSERVABLE SYMPTOMATIC BENEFIT, THE PATIENT WHO FAILS TO SHOW SUBSTANTIAL CLINICAL BENEFIT WITHIN 3 WEEKS OF INITIATION OF TREATMENT, SHOULD BE WITHDRAWN FROM TASMAR.

TASMAR therapy should not be initiated if the patient exhibits clinical evidence of liver disease or two SGPT/ALT or SGOT/AST values greater than the upper limit of normal. Patients with severe dyskinesia or dystonia should be treated with caution (see PRECAUTIONS: Rhabdomyolysis).

Patients who develop evidence of hepatocellular injury while on TASMAR and are withdrawn from the drug for any reason may be at increased risk for liver injury if TASMAR is reintroduced. These patients should not ordinarily be considered for retreatment with TASMAR.

Only prescribe TASMAR for patients taking concomitant carbidopa levodopa therapy. The initial dose of TASMAR is always 100 mg three times per day. The recommended daily dose of TASMAR is also 100 mg tid. In clinical trials, elevations in ALT occurred more frequently at the dose of 200 mg tid. While it is unknown whether the risk of acute fulminant liver failure is increased at the 200-mg dose, it would be prudent to use 200 mg only if the anticipated incremental clinical benefit is justified (see BOXED WARNING, WARNINGS, and PRECAUTIONS: Laboratory Tests). If a patient fails to show the expected incremental benefit on the 200-mg dose after a total of 3 weeks of treatment (regardless of dose), TASMAR should be discontinued.

In clinical trials, the first dose of the day of TASMAR was always taken together with the first dose of the day of levodopa/carbidopa, and the subsequent doses of TASMAR were given approximately 6 and 12 hours later.

In clinical trials, the majority of patients required a decrease in their daily levodopa dose if their daily dose of levodopa was >600 mg or if patients had moderate or severe dyskinesias before beginning treatment.

To optimize an individual patient's response, reductions in daily levodopa dose may be necessary. In clinical trials, the average reduction in daily levodopa dose was about 30% in those patients requiring a levodopa dose reduction. (Greater than 70% of patients with levodopa doses above 600 mg daily required such a reduction.)

TASMAR can be combined with both the immediate and sustained release formulations of levodopa/carbidopa.

TASMAR may be taken with or without food (see CLINICAL PHARMACOLOGY).

Patients With Impaired Hepatic Function:

TASMAR therapy should not be initiated in any patient with liver disease or two SGPT/ALT or SGOT/AST values greater than the upper limit of normal. (see BOXED WARNING, WARNINGS, and CLINICAL PHARMACOLOGY.)

Patients With Impaired Renal Function:

No dose adjustment of TASMAR is recommended for patients with mild to moderate renal impairment. However, patients with severe renal impairment should be treated with caution. The safety of tolcapone has not been examined in subjects who had creatinine clearance less than 25 mL/min (see CLINICAL PHARMACOLOGY).

Withdrawing Patients From TASMAR:

As with any dopaminergic drug, withdrawal or abrupt reduction in the TASMAR dose may lead to emergence of signs and symptoms of Parkinson's disease or Hyperpyrexia and Confusion, a syndrome complex resembling the neuroleptic malignant syndrome (see PRECAUTIONS: Events Reported With Dopaminergic Therapy). If a decision is made to discontinue treatment with TASMAR, then it is recommended to closely monitor the patient and adjust other dopaminergic treatments as needed. This syndrome should be considered in the differential diagnosis for any patient who develops a high fever or severe rigidity. Tapering TASMAR has not been systematically evaluated. As the duration of COMT inhibition with TASMAR is generally 5 to 6 hours on average, decreasing the frequency of dosage to twice or once a day may not in itself prevent withdrawal effects.

HOW SUPPLIED:

TASMAR is supplied as film-coated tablets containing 100 mg tolcapone. The 100 mg beige to yellowish beige tablet is hexagonal and biconvex. Debossed on one side of the 100 mg tablet is TASMAR and the tablet strength (100), on the other side is a V.

TASMAR 100 mg Tablets: bottles of 90 (NDC 0187-0938-01).

Storage:

Store in tight containers at 20° to 25°C (68° to 77°F); excursions permitted to 15° to 30°C (59° to 86°F) [see USP Controlled Room Temperature].

Distributed by:
Bausch Health US, LLC
Bridgewater, NJ 08807 USA

Manufactured by:
Bausch Health Companies Inc.
Steinbach, MB R5G 1Z7, Canada

TASMAR is a trademark of Bausch Health Companies Inc. or its affiliates.

© 2020 Bausch Health Companies Inc. or its affiliates

PATIENT ACKNOWLEDGEMENT OF RISKS

ASSOCIATED WITH TASMAR TREATMENT

The following is important information that patients should know about TASMAR.

- TASMAR should not be used until you and your doctor (insert physician name here: _________________________) have had a complete discussion about the risks and benefits associated with the use of TASMAR.
- Reports of potentially life-threatening cases of severe hepatocellular injury, including fulminant liver failure resulting in death, have been reported in association with use of TASMAR.
- There are no laboratory tests that will predict in advance which patients are at an increased risk for liver failure or death from liver failure.
- Patients should have the recommended liver blood tests before treatment with TASMAR is begun and periodically for the first 6 months of therapy. After the first six months, periodic liver blood tests should be performed as directed by your physician. If the dose of TASMAR is to be increased, the liver blood tests should be checked before increasing the dose and repeated periodically as described earlier. Liver blood tests may help detect if liver failure has occurred but they may do so only after significant damage, that may not go away, has already occurred.
- Patients must immediately report any unusual symptoms to their physician and be especially aware of persistent nausea, fatigue, lethargy, decreased appetite, jaundice (yellowing of skin or the whites of the eyes), dark urine, itchiness or right-sided abdominal pain.

The above points of information, possibly along with other information, have been explained to me and I have been able to ask my physician questions and discuss risks and benefits associated with TASMAR treatment.

Patient or Patient Caregiver Signature:___________________________________________________

Date: ________________________________

NOTE TO PHYSICIAN: It is strongly recommended that you retain a signed copy of this form with the patient's medical records.

SUPPLY OF PATIENT ACKNOWLEDGEMENT FORMS:

A supply of Patient Acknowledgement forms is available, free of charge, from your local Bausch Health representative, by calling 1-800-321-4576. Permission to use the above Patient Acknowledgement form by photocopy reproduction is also hereby granted by Bausch Health US, LLC.

Rev. 10/2020
20003004
9467003

PRINCIPAL DISPLAY PANEL - 100 mg Tablet Bottle Label

NDC 0187-0938-01
Rx Only

Tasmar ®
(tolcapone) Tablets

90 Tablets

100 mg

Each tablet contains
100 mg tolcapone

BAUSCH Health